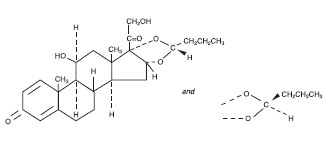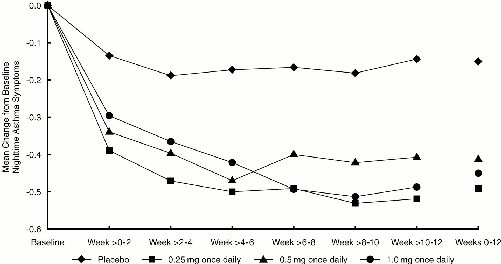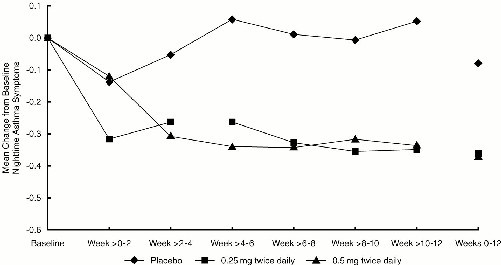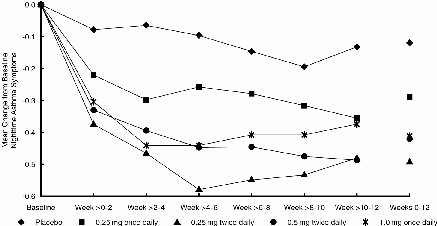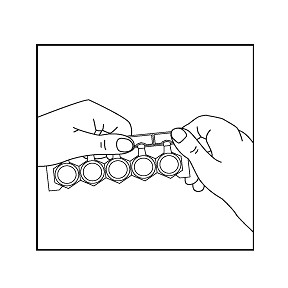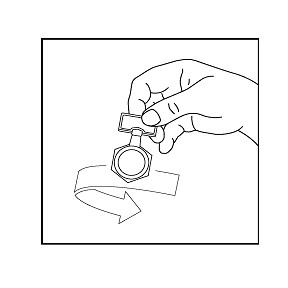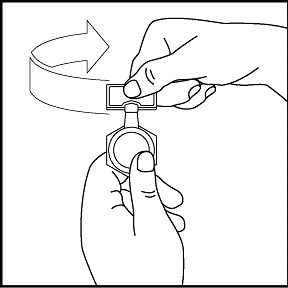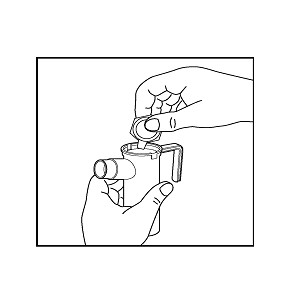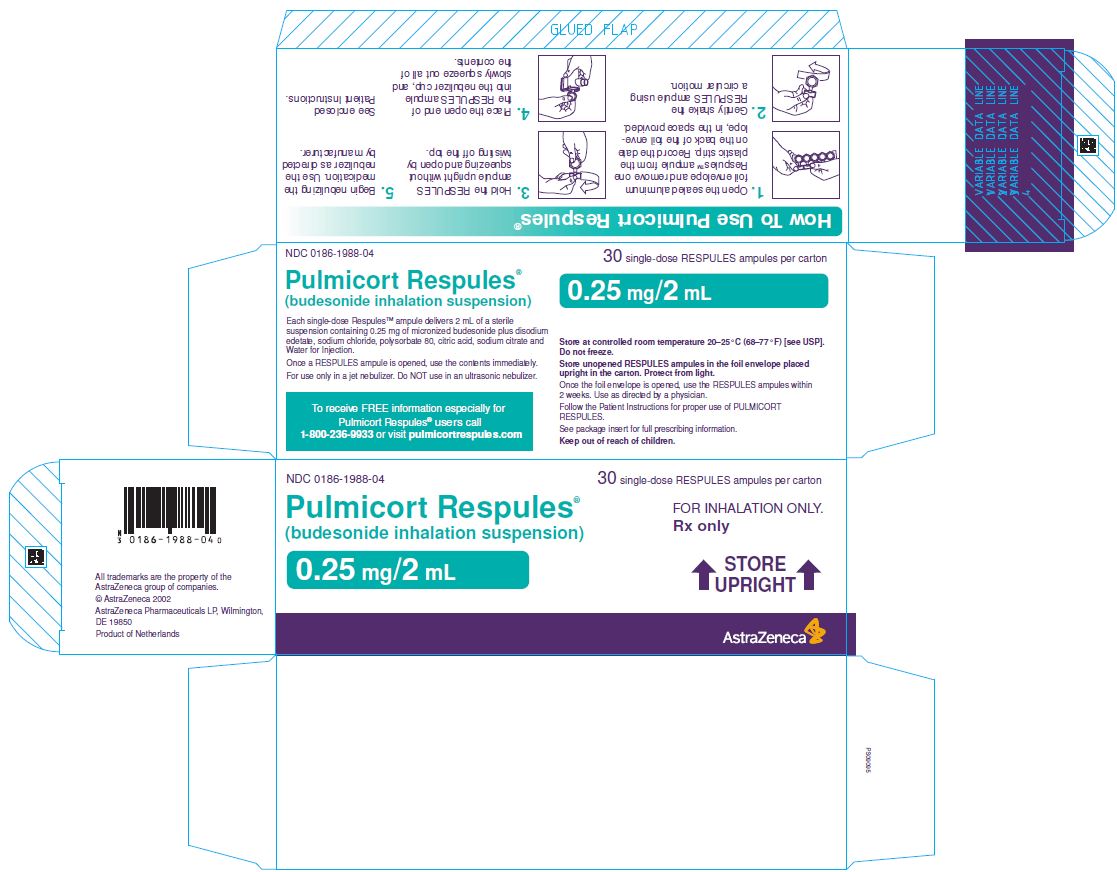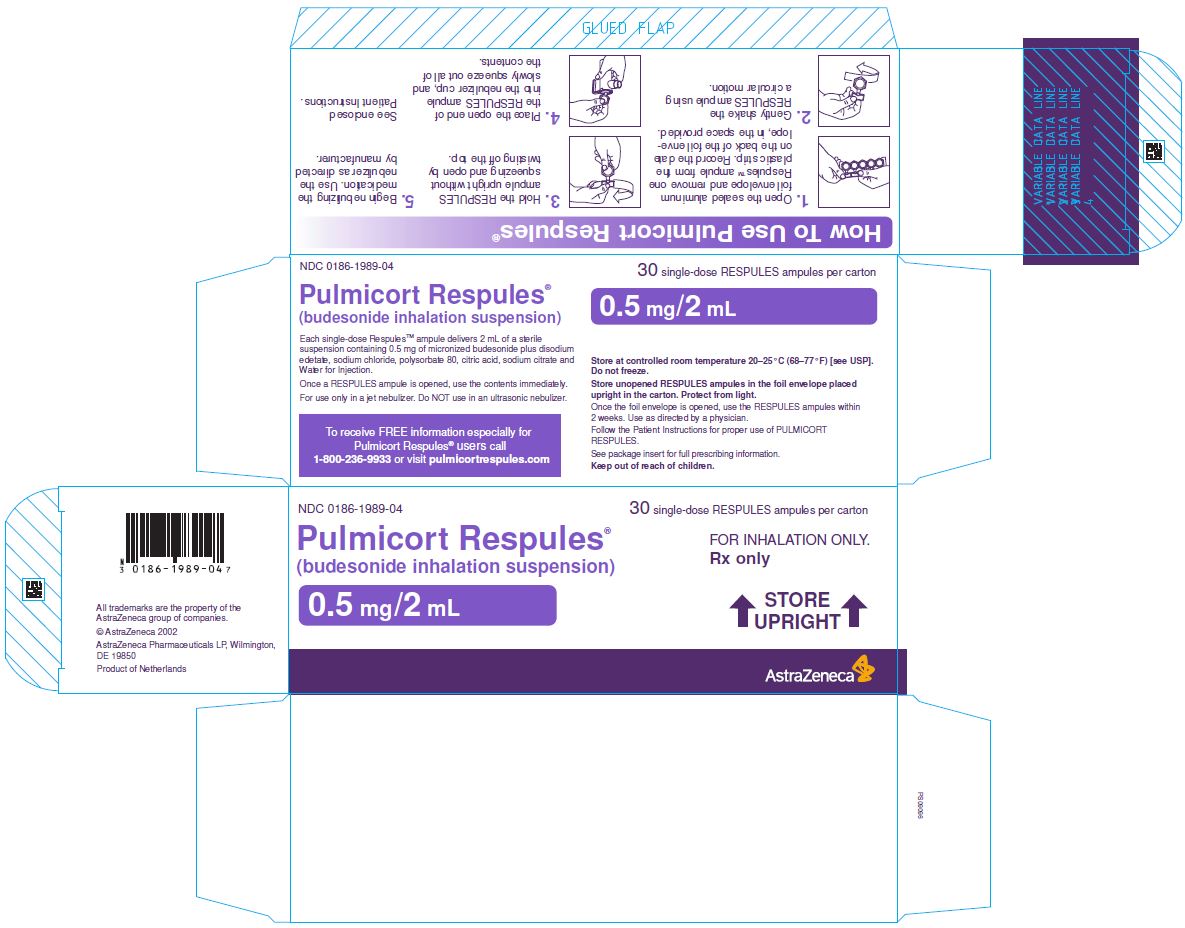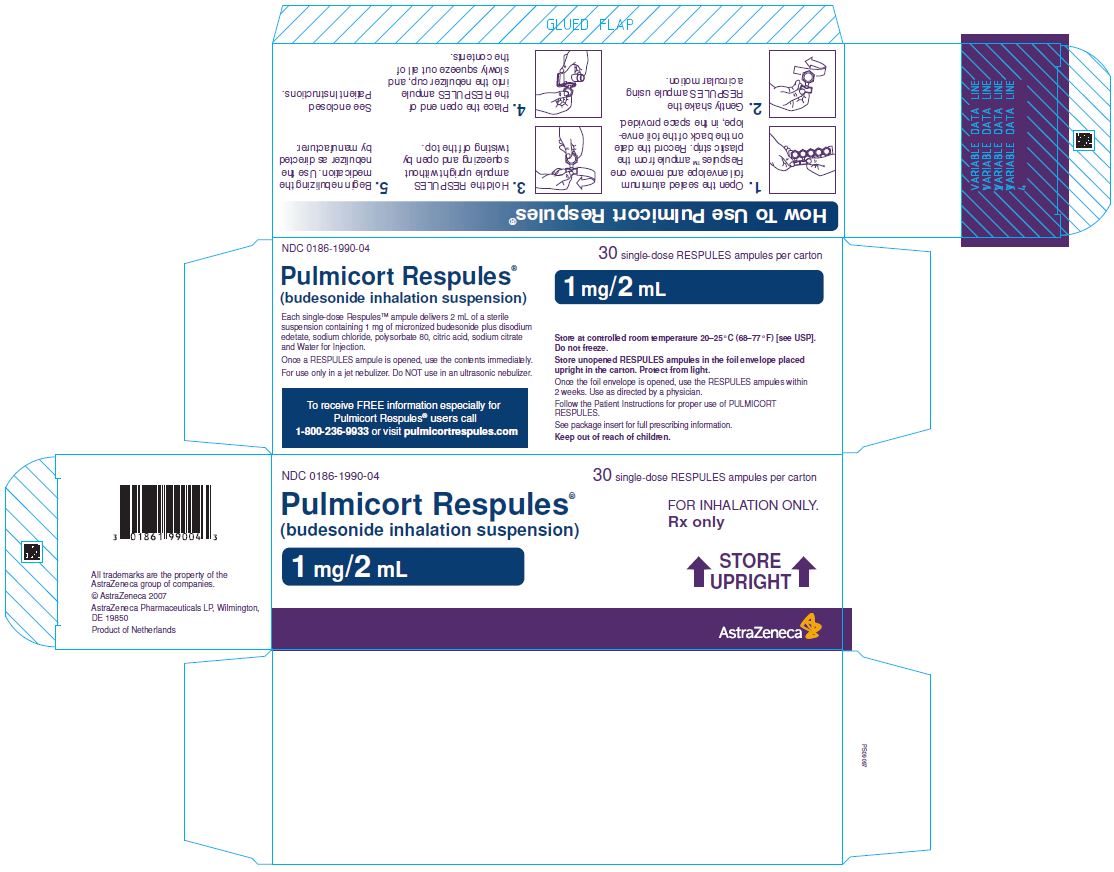 DRUG LABEL: PULMICORT RESPULES
NDC: 0186-1988 | Form: SUSPENSION
Manufacturer: AstraZeneca Pharmaceuticals LP
Category: prescription | Type: HUMAN PRESCRIPTION DRUG LABEL
Date: 20191011

ACTIVE INGREDIENTS: BUDESONIDE 0.25 mg/2 mL
INACTIVE INGREDIENTS: EDETATE DISODIUM; SODIUM CHLORIDE; SODIUM CITRATE, UNSPECIFIED FORM; POLYSORBATE 80; WATER; ANHYDROUS CITRIC ACID

HIGHLIGHTS OF PRESCRIBING INFORMATION

These highlights do not include all the information needed to use PULMICORT RESPULES® safely and effectively. See full prescribing information for PULMICORT RESPULES®.
PULMICORT RESPULES® (budesonide) inhalation suspension
Initial U.S. Approval: 2000

1 INDICATIONS AND USAGE

PULMICORT RESPULES® is an inhaled corticosteroid indicated for:

- Maintenance treatment of asthma and as prophylactic therapy in children 12 months to 8 years of age (1)

Limitations of Use:

Not indicated for the relief of acute bronchospasm (1)

2 DOSAGE AND ADMINISTRATION

Recommended dosing based on previous therapy (2). Start with the lowest recommended dose:

- Bronchodilators alone: 0.5 mg once daily or 0.25 mg twice daily
- Inhaled corticosteroids: 0.5 mg once daily or 0.25 mg twice daily up to 0.5 mg twice daily
- Oral corticosteroids: 0.5 mg twice daily or 1 mg once daily
- In symptomatic children not responding to non-steroidal therapy, a starting dose of 0.25 mg once daily may be considered
- If once-daily treatment does not provide adequate control, the total daily dose should be increased and/or administered as a divided dose. Once asthma stability is achieved, titrate the dose downwards
- For inhalation use via compressed air driven jet nebulizers only (not for use with ultrasonic devices). Not for injection. (2.2)

3 DOSAGE FORMS AND STRENGTHS

Inhalation suspension: 0.25 mg/2 mL, 0.5 mg/2 mL, 1 mg/2 mL (3)

4 CONTRAINDICATIONS

- Primary treatment of status asthmaticus or other acute episodes of asthma where intensive measures are required (4)
- Hypersensitivity to any of the ingredients in PULMICORT RESPULES (4)

5 WARNINGS AND PRECAUTIONS

- Localized Infections: Candida albicans infection of the mouth and throat may occur. Monitor patients periodically for signs of adverse effects on the oral cavity. Advise patients to rinse the mouth following inhalation (5.1)
- Deterioration of Disease and Acute Asthma Episodes: Do not use for the relief of acute bronchospasm (5.2)
- Hypersensitivity Reactions: Anaphylaxis, rash, contact dermatitis, urticaria, angioedema, and bronchospasm have been reported with use of PULMICORT RESPULES. Discontinue PULMICORT RESPULES if such reactions occur (5.3)
- Immunosuppression: Potential worsening of infections (e.g., existing tuberculosis, fungal, bacterial, viral, or parasitic infection; or ocular herpes simplex). Use with caution in patients with these infections. More serious or even fatal course of chickenpox or measles can occur in susceptible patients (5.4)
- Transferring Patients from Systemic Corticosteroid Therapy: Risk of impaired adrenal function when transferring from oral steroids. Taper patients slowly from systemic corticosteroids if transferring to PULMICORT RESPULES (5.5)
- Hypercorticism and Adrenal Suppression: May occur with very high dosages or at the regular dosage in susceptible individuals. If such changes occur, reduce PULMICORT RESPULES slowly (5.6)
- Reduction in Bone Mineral Density with Long-term Administration: Monitor patients with major risk factors for decreased bone mineral content (5.7)
- Effects on Growth: Monitor growth of pediatric patients (5.8)
- Glaucoma and Cataracts: Close monitoring is warranted (5.9)
- Paradoxical Bronchospasm: Discontinue PULMICORT RESPULES and institute alternative therapy if paradoxical bronchospasm occurs (5.10)
- Eosinophilic Conditions and Churg-Strauss Syndrome: Be alert to eosinophilic conditions (5.11)

6 ADVERSE REACTIONS

Most common adverse reactions (incidence >3%) are respiratory infection, rhinitis, coughing, otitis media, viral infection, moniliasis, gastroenteritis, vomiting, diarrhea, abdominal pain, ear infection, epistaxis, conjunctivitis, rash (6.1)

To report SUSPECTED ADVERSE REACTIONS, contact AstraZeneca at 1–800–236–9933 or FDA at 1-800-FDA-1088 or www.fda.gov/medwatch

7 DRUG INTERACTIONS

Strong Cytochrome P450 3A4 Inhibitors (e.g., ritonavir): Use with caution. May cause increased systemic corticosteroid effects (5.12, 7.1)

FULL PRESCRIBING INFORMATION

1 INDICATIONS AND USAGE

1.1 Maintenance Treatment of Asthma

PULMICORT RESPULES is indicated for the maintenance treatment of asthma and as prophylactic therapy in children 12 months to 8 years of age.

Limitations of Use:

- PULMICORT RESPULES is NOT indicated for the relief of acute bronchospasm.

2 DOSAGE AND ADMINISTRATION

The recommended starting dose and highest recommended dose of PULMICORT RESPULES, based on prior asthma therapy, are listed in the following table.

Previous Therapy | Recommended Starting Dose | Highest Recommended Dose
Bronchodilators alone | 0.5 mg total daily dose administered either once daily or twice daily in divided doses | 0.5 mg total daily dose
Inhaled Corticosteroids | 0.5 mg total daily dose administered either once daily or twice daily in divided doses | 1 mg total daily dose
Oral Corticosteroids | 1 mg total daily dose administered either as 0.5 mg twice daily or 1 mg once daily | 1 mg total daily dose

2.1 Dosing Recommendations

Dosing recommendations based on previous therapy are as follows:

- Bronchodilators alone: 0.5 mg once daily or 0.25 mg twice daily
- Inhaled corticosteroids: 0.5 mg once daily or 0.25 mg twice daily up to 0.5 mg twice daily
- Oral corticosteroids: 0.5 mg twice daily or 1 mg once daily

In symptomatic children not responding to non-steroidal therapy, a starting dose of 0.25 mg once daily may be considered. If once-daily treatment does not provide adequate control, the total daily dose should be increased and/or administered as a divided dose. In all patients, it is desirable to downward-titrate to the lowest effective dose once asthma stability is achieved.

2.2 Directions for Use

PULMICORT RESPULES should be administered via jet nebulizer connected to an air compressor with an adequate air flow, equipped with a mouthpiece or suitable face mask. Ultrasonic nebulizers are not suitable for the adequate administration of PULMICORT RESPULES and, therefore, are NOT recommended.

The effects of mixing PULMICORT RESPULES with other nebulizable medications have not been adequately assessed. PULMICORT RESPULES should be administered separately in the nebulizer [see Patient Counseling Information (17.1)].

A Pari-LC-Jet Plus Nebulizer (with face mask or mouthpiece) connected to a Pari Master compressor was used to deliver PULMICORT RESPULES to each patient in 3 U.S. controlled clinical studies. The safety and efficacy of PULMICORT RESPULES delivered by other nebulizers and compressors have not been established.

3 DOSAGE FORMS AND STRENGTHS

PULMICORT RESPULES is available in three strengths, each containing 2 mL: 0.25 mg/2 mL, 0.5 mg/2 mL, and 1 mg/2 mL. PULMICORT RESPULES is supplied in sealed aluminum foil envelopes containing one plastic strip of five single-dose RESPULES ampules together with patient instructions for use. There are 30 RESPULES ampules in a carton. Each single-dose RESPULES ampule contains 2 mL of sterile liquid suspension.

4 CONTRAINDICATIONS

The use of PULMICORT RESPULES is contraindicated in the following conditions:

- Primary treatment of status asthmaticus or other acute episodes of asthma where intensive measures are required.
- Hypersensitivity to budesonide or any of the ingredients of PULMICORT RESPULES [see Warnings and Precautions (5.3), Description (11), Adverse Reactions (6.2)].

5 WARNINGS AND PRECAUTIONS

5.1 Local Effects

In clinical trials with PULMICORT RESPULES, localized infections with Candida albicans occurred in the mouth and pharynx in some patients. The incidences of localized infections of Candida albicans were similar between the placebo and PULMICORT RESPULES treatment groups. If these infections develop, they may require treatment with appropriate local or systemic antifungal therapy and/or discontinuance of treatment with PULMICORT RESPULES. Patients should rinse the mouth after inhalation of PULMICORT RESPULES.

5.2 Deterioration of Disease and Acute Asthma Episodes

PULMICORT RESPULES is not a bronchodilator and is not indicated for the rapid relief of acute bronchospasm or other acute episodes of asthma.

Patients should be instructed to contact their physician immediately if episodes of asthma not responsive to their usual doses of bronchodilators occur during the course of treatment with PULMICORT RESPULES. During such episodes, patients may require therapy with oral corticosteroids.

5.3 Hypersensitivity Reactions Including Anaphylaxis

Hypersensitivity reactions including anaphylaxis, rash, contact dermatitis, urticaria, angioedema, and bronchospasm have been reported with use of PULMICORT RESPULES. Discontinue PULMICORT RESPULES if such reactions occur [see Contraindications (4)].

5.4 Immunosuppression

Patients who are on drugs that suppress the immune system are more susceptible to infection than healthy individuals. Chicken pox and measles, for example, can have a more serious or even fatal course in susceptible children or adults using corticosteroids. In children or adults who have not had these diseases, or been properly immunized, particular care should be taken to avoid exposure. How the dose, route, and duration of corticosteroid administration affect the risk of developing a disseminated infection is not known. The contribution of the underlying disease and/or prior corticosteroid treatment to the risk is also not known. If exposed to chicken pox, therapy with varicella zoster immune globulin (VZIG) or pooled intravenous immunoglobulin (IVIG), as appropriate, may be indicated. If exposed to measles, prophylaxis with pooled intramuscular immunoglobulin (IG) may be indicated (see the respective package inserts for complete VZIG and IG prescribing information). If chicken pox develops, treatment with antiviral agents may be considered.

The clinical course of chicken pox or measles infection in patients on inhaled corticosteroids has not been studied. However, a clinical study has examined the immune responsiveness of asthma patients 12 months to 8 years of age who were treated with PULMICORT RESPULES. An open-label non-randomized clinical study examined the immune responsiveness of varicella vaccine in 243 asthma patients 12 months to 8 years of age who were treated with PULMICORT RESPULES 0.25 mg to 1 mg daily (n=151) or non-corticosteroid asthma therapy (n=92) (i.e., beta2-agonists, leukotriene receptor antagonists, cromones). The percentage of patients developing a seroprotective antibody titer of ≥5.0 (gpELISA value) in response to the vaccination was similar in patients treated with PULMICORT RESPULES (85%) compared to patients treated with non-corticosteroid asthma therapy (90%). No patient treated with PULMICORT RESPULES developed chicken pox as a result of vaccination.

Inhaled corticosteroids should be used with caution, if at all, in patients with active or quiescent tuberculosis infection of the respiratory tract, untreated systemic fungal, bacterial, viral, or parasitic infections; or ocular herpes simplex.

5.5 Transferring Patients from Systemic Corticosteroid Therapy

Particular care is needed for patients who are transferred from systemically active corticosteroids to inhaled corticosteroids because deaths due to adrenal insufficiency have occurred in asthmatic patients during and after transfer from systemic corticosteroids to less systemically available inhaled corticosteroids. After withdrawal from systemic corticosteroids, a number of months are required for recovery of hypothalamic-pituitary-adrenal (HPA)-axis function.

Patients who have been previously maintained on 20 mg or more per day of prednisone (or its equivalent) may be most susceptible, particularly when their systemic corticosteroids have been almost completely withdrawn.

During this period of HPA-axis suppression, patients may exhibit signs and symptoms of adrenal insufficiency when exposed to trauma, surgery, infection (particularly gastroenteritis) or other conditions associated with severe electrolyte loss. Although PULMICORT RESPULES may provide control of asthma symptoms during these episodes, in recommended doses it supplies less than normal physiological amounts of glucocorticosteroid systemically and does NOT provide the mineralocorticoid activity that is necessary for coping with these emergencies.

During periods of stress or a severe asthma attack, patients who have been withdrawn from systemic corticosteroids should be instructed to resume oral corticosteroids (in large doses) immediately and to contact their physicians for further instructions. These patients should also be instructed to carry a medical identification card indicating that they may need supplementary systemic corticosteroids during periods of stress or a severe asthma attack.

Patients requiring oral corticosteroids should be weaned slowly from systemic corticosteroid use after transferring to PULMICORT RESPULES. Initially, PULMICORT RESPULES should be used concurrently with the patient’s usual maintenance dose of systemic corticosteroid. After approximately one week, gradual withdrawal of the systemic corticosteroid may be initiated by reducing the daily or alternate daily dose. Further incremental reductions may be made after an interval of one or two weeks, depending on the response of the patient. Generally, these decrements should not exceed 25% of the prednisone dose or its equivalent. A slow rate of withdrawal is strongly recommended.

Lung function (FEV1 or AM PEF), beta-agonist use, and asthma symptoms should be carefully monitored during withdrawal of oral corticosteroids. In addition to monitoring asthma signs and symptoms, patients should be observed for signs and symptoms of adrenal insufficiency such as fatigue, lassitude, weakness, nausea and vomiting, and hypotension.

Transfer of patients from systemic corticosteroid therapy to PULMICORT RESPULES may unmask allergic or other immunologic conditions previously suppressed by the systemic corticosteroid therapy, e.g., rhinitis, conjunctivitis, eosinophilic conditions, eczema, and arthritis [see Dosage and Administration (2)].

During withdrawal from oral corticosteroids, patients may experience symptoms of systemically active corticosteroid withdrawal (e.g., joint and/or muscular pain, lassitude, depression) despite maintenance or even improvement of respiratory function.

5.6 Hypercorticism and Adrenal Suppression

PULMICORT RESPULES, will often help control asthma symptoms with less suppression of HPA function than therapeutically equivalent oral doses of prednisone. Since individual sensitivity to effects on cortisol production exists, physicians should consider this information when prescribing PULMICORT RESPULES. Because of the possibility of systemic absorption of inhaled corticosteroids, patients treated with PULMICORT RESPULES should be observed carefully for any evidence of systemic corticosteroid effects. Particular care should be taken in observing patients post-operatively or during periods of stress for evidence of inadequate adrenal response. It is possible that systemic corticosteroid effects such as hypercorticism, and adrenal suppression (including adrenal crisis) may appear in a small number of patients, particularly when budesonide is administered at higher than recommended doses over prolonged periods of time. If such effects occur, the dosage of PULMICORT RESPULES should be reduced slowly, consistent with accepted procedures for tapering of systemic corticosteroids and for management of asthma.

5.7 Reduction in Bone Mineral Density

Decreases in bone mineral density (BMD) have been observed with long-term administration of products containing inhaled corticosteroids. The clinical significance of small changes in BMD with regard to long-term outcomes is unknown. Patients with major risk factors for decreased bone mineral content, such as prolonged immobilization, family history of osteoporosis, poor nutrition, or chronic use of drugs that can reduce bone mass (e.g., anticonvulsants and corticosteroids), should be monitored and treated with established standards of care.

5.8 Effects on Growth

Orally inhaled corticosteroids, including budesonide, may cause a reduction in growth velocity when administered to pediatric patients. Monitor the growth of pediatric patients receiving PULMICORT RESPULES routinely (e.g., via stadiometry). To minimize the systemic effects of orally inhaled corticosteroids, including PULMICORT RESPULES, each patient should be titrated to his/her lowest effective dose [see Use in Specific Populations (8.4)].

5.9 Glaucoma and Cataracts

Glaucoma, increased intraocular pressure, and cataracts have been reported following the long-term administration of inhaled corticosteroids, including budesonide. Therefore, close monitoring is warranted in patients with a change in vision or with a history of increased intraocular pressure, glaucoma, and/or cataracts.

5.10 Paradoxical Bronchospasm and Upper Airway Symptoms

As with other inhaled asthma medications, bronchospasm, with an immediate increase in wheezing, may occur after dosing. If acute bronchospasm occurs following dosing with PULMICORT RESPULES, it should be treated immediately with a fast-acting inhaled bronchodilator. Treatment with PULMICORT RESPULES should be discontinued and alternate therapy instituted.

5.11 Eosinophilic Conditions and Churg-Strauss Syndrome

In rare cases, patients on inhaled corticosteroids may present with systemic eosinophilic conditions. Some of these patients have clinical features of vasculitis consistent with Churg-Strauss syndrome, a condition that is often treated with systemic corticosteroids therapy. These events usually, but not always, have been associated with the reduction and/or withdrawal of oral corticosteroid therapy following the introduction of inhaled corticosteroids. Healthcare providers should be alert to eosinophilia, vasculitis rash, worsening pulmonary symptoms, cardiac complications, and/or neuropathy presenting in their patients. A causal relationship between budesonide and these underlying conditions has not been established.

5.12 Drug Interactions with Strong Cytochrome P450 3A4 Inhibitors

Caution should be exercised when considering the coadministration of PULMICORT RESPULES with ketoconazole, and other known strong CYP3A4 inhibitors (e.g., ritonavir, atazanavir, clarithromycin, indinavir, itraconazole, nefazodone, nelfinavir, saquinavir, telithromycin) because adverse effects related to increased systemic exposure to budesonide may occur [see Drug Interactions (7.1), Clinical Pharmacology (12.3)].

6 ADVERSE REACTIONS

Systemic and inhaled corticosteroid use may result in the following:

- Candida albicans Infection [see Warnings and Precautions (5.1)]
- Hypersensitivity Reactions Including Anaphylaxis [see Warnings and Precautions (5.3)]
- Immunosuppression [see Warnings and Precautions (5.4)]
- Hypercorticism and Adrenal Suppression [see Warnings and Precautions (5.6)]
- Reduction in Bone Mineral Density [see Warnings and Precautions (5.7)]
- Growth Effects in Pediatric Patients [see Warnings and Precautions (5.8), Use in Specific Populations (8.4)]
- Glaucoma, Increased Intraocular Pressure and Cataracts [see Warnings and Precautions (5.9)]
- Eosinophilic Conditions and Churg-Strauss Syndrome [see Warnings and Precautions (5.11)]

6.1 Clinical Trials Experience

Because clinical trials are conducted under widely varying conditions, adverse reaction rates observed in the clinical trials of a drug cannot be directly compared to rates in the clinical trials of another drug and may not reflect the rates observed in practice.

The incidence of common adverse reactions is based on three double-blind, placebo-controlled, randomized U.S. clinical trials in which 945 patients, 12 months to 8 years of age, (98 patients ≥12 months and <2 years of age; 225 patients ≥2 and <4 years of age; and 622 patients ≥4 and ≤8 years of age) were treated with PULMICORT RESPULES (0.25 to 1 mg total daily dose for 12 weeks) or vehicle placebo. The incidence and nature of adverse events reported for PULMICORT RESPULES was comparable to that reported for placebo. The following table shows the incidence of adverse events in U.S. controlled clinical trials, regardless of relationship to treatment, in patients previously receiving bronchodilators and/or inhaled corticosteroids. This population included a total of 605 male and 340 female patients and 78.4% were Caucasian, 13.8% African American, 5.5% Hispanic and 2.3% Other.

Table 1 – Adverse Reactions occurring at an incidence of ≥3% in at least one active treatment group where the incidence was higher with PULMICORT RESPULES than placebo
Adverse Events | Vehicle Placebo; (n=227); % | PULMICORT RESPULES; Total Daily Dose
Adverse Events | Vehicle Placebo; (n=227); % | 0.25 mg; (n=178); % | 0.5 mg; (n=223); % | 1 mg; (n=317); %
Respiratory System Disorder
Respiratory Infection | 36 | 34 | 35 | 38
Rhinitis | 9 | 7 | 11 | 12
Coughing | 5 | 5 | 9 | 8
Resistance Mechanism Disorders
Otitis Media | 11 | 12 | 11 | 9
Viral Infection | 3 | 4 | 5 | 3
Moniliasis | 2 | 4 | 3 | 4
Gastrointestinal System Disorders
Gastroenteritis | 4 | 5 | 5 | 5
Vomiting | 3 | 2 | 4 | 4
Diarrhea | 2 | 4 | 4 | 2
Abdominal Pain | 2 | 3 | 2 | 3
Hearing and Vestibular Disorders
Ear Infection | 4 | 2 | 4 | 5
Platelet, Bleeding and Clotting Disorders
Epistaxis | 1 | 2 | 4 | 3
Vision Disorders
Conjunctivitis | 2 | <1 | 4 | 2
Skin and Appendages Disorders
Rash | 3 | <1 | 4 | 2

The information below includes all adverse reactions by system organ class with an incidence of 1 to < 3%, in at least one PULMICORT RESPULES treatment group where the incidence was higher with PULMICORT RESPULES than with placebo, regardless of relationship to treatment.

Blood and lymphatic system disorders: cervical lymphadenopathy

Ear and labyrinth disorders: earache

General disorders and administration site conditions: fatigue, flu-like disorder

Immune system disorders: allergic reaction

Infections and infestations: eye infection, herpes simplex, external ear infection, infection

Injury, poisoning and procedural complication: fracture

Metabolism and nutrition disorders: anorexia

Musculoskeletal and connective tissue disorders: myalgia

Nervous system disorders: hyperkinesia

Psychiatric disorders: emotional lability

Respiratory, thoracic, and mediastinal disorders: chest pain, dysphonia, stridor

Skin and subcutaneous tissue disorders: contact dermatitis, eczema, pustular rash, pruritus, purpura

The incidence of reported adverse events was similar between the 447 PULMICORT RESPULES-treated (mean total daily dose 0.5 to 1 mg) and 223 conventional therapy-treated pediatric asthma patients followed for one year in three open-label studies.

6.2 Postmarketing Experience

The following adverse reactions have been reported during post-approval use of PULMICORT RESPULES. Because these reactions are reported voluntarily from a population of uncertain size, it is not always possible to reliably estimate their frequency or establish a causal relationship to drug exposure. Some of these adverse reactions may also have been observed in clinical studies with PULMICORT RESPULES.

Endocrine disorders: symptoms of hypocorticism and hypercorticism [see Warnings and Precautions (5.6)]

Eye disorders: cataracts, glaucoma, increased intraocular pressure [see Warnings and Precautions (5.9)]

General disorders and administration site conditions: fever, pain

Immune system disorders: immediate and delayed hypersensitivity reactions including, anaphylaxis, angioedema, bronchospasm, rash, contact dermatitis, and urticaria [see Contraindications (4), Warnings and Precautions (5.10)]

Infection and Infestation: sinusitis, pharyngitis, bronchitis

Musculoskeletal and connective tissue disorders: avascular necrosis of the femoral head, osteoporosis, growth suppression

Nervous system disorders: headache

Psychiatric disorders: psychiatric symptoms including psychosis, depression, aggressive reactions, irritability, nervousness, restlessness, and anxiety

Respiratory, thoracic, and mediastinal disorders: cough, dysphonia and throat irritation

Skin and subcutaneous tissue disorders: skin bruising, facial skin irritation

Cases of growth suppression have been reported for inhaled corticosteroids including post-marketing reports for PULMICORT RESPULES [see Warnings and Precautions (5.8), Use in Specific Populations (8.4)].

7 DRUG INTERACTIONS

7.1 Inhibitors of Cytochrome P450 3A4

The main route of metabolism of corticosteroids, including budesonide, is via cytochrome P450 (CYP) isoenzyme 3A4 (CYP3A4). After oral administration of ketoconazole, a strong inhibitor of CYP3A4, the mean plasma concentration of orally administered budesonide increased. Concomitant administration of a CYP3A4 inhibitor may inhibit the metabolism of, and increase the systemic exposure to, budesonide. Caution should be exercised when considering the coadministration of PULMICORT RESPULES with long-term ketoconazole and other known strong CYP3A4 inhibitors (e.g., ritonavir, atazanavir, clarithromycin, indinavir, itraconazole, nefazodone, nelfinavir, saquinavir, telithromycin) [see Warnings and Precautions (5.12), Clinical Pharmacology (12.3)].

8 USE IN SPECIFIC POPULATIONS

8.1 Pregnancy

Risk Summary

There are no adequate well-controlled studies of PULMICORT RESPULES in pregnant women. However, there are published studies on the use of budesonide, the active ingredient in PULMICORT RESPULES, in pregnant women. In animal reproduction studies, budesonide, administered by the subcutaneous route, caused structural abnormalities, was embryocidal, and reduced fetal weights in rats and rabbits at less than the maximum recommended human daily inhalation dose (MRHDID), but these effects were not seen in rats that received inhaled doses approximately 2 times the MRHDID (see Data). Studies of pregnant women have not shown that inhaled budesonide increases the risk of abnormalities when administered during pregnancy. Experience with oral corticosteroids suggests that rodents are more prone to structural abnormalities from corticosteroid exposure than humans.

The estimated background risk of major birth defects and miscarriage of the indicated populations is unknown. In the U.S. general population, the estimated background risk of major birth defects and miscarriage in clinically recognized pregnancies is 2% to 4% and 15% to 20%, respectively.

Clinical Considerations

Disease-Associated Maternal and/or Embryo/Fetal risk

In women with poorly or moderately controlled asthma, there is an increased risk of several perinatal adverse outcomes such as preeclampsia in the mother and prematurity, low birth weight, and small for gestational age in the neonate. Pregnant women with asthma should be closely monitored and medication adjusted as necessary to maintain optimal asthma control.

Labor or Delivery

There are no well-controlled human studies that have investigated the effects of PULMICORT RESPULES during labor and delivery.

Data

Human Data

Studies of pregnant women have not shown that inhaled budesonide increases the risk of abnormalities when administered during pregnancy. The results from a large population-based prospective cohort epidemiological study reviewing data from three Swedish registries covering approximately 99% of the pregnancies from 1995-1997 (i.e., Swedish Medical Birth Registry; Registry of Congenital Malformations; Child Cardiology Registry) indicate no increased risk for congenital malformations from the use of inhaled budesonide during early pregnancy. Congenital malformations were studied in 2014 infants born to mothers reporting the use of inhaled budesonide for asthma in early pregnancy (usually 10-12 weeks after the last menstrual period), the period when most major organ malformations occur. The rate of recorded congenital malformations was similar compared to the general population rate (3.8% vs. 3.5%, respectively). In addition, after exposure to inhaled budesonide, the number of infants born with orofacial clefts was similar to the expected number in the normal population (4 children vs. 3.3, respectively).

These same data were utilized in a second study bringing the total to 2534 infants whose mothers were exposed to inhaled budesonide. In this study, the rate of congenital malformations among infants whose mothers were exposed to inhaled budesonide during early pregnancy was not different from the rate for all newborn babies during the same period (3.6%).

Animal Data

In a fertility and reproduction study, male rats were subcutaneously dosed for 9 weeks and females for 2 weeks prior to pairing and throughout the mating period. Females were dosed up until weaning of their offspring. Budesonide caused a decrease in prenatal viability and viability in the pups at birth and during lactation, along with a decrease in maternal body-weight gain, at doses 0.2 times the MRHDID (on a mcg/m^2 basis at maternal subcutaneous doses of 20 mcg/kg/day and above). No such effects were noted at a dose 0.05 times the MRHDID (on a mcg/m^2 basis at a maternal subcutaneous dose of 5 mcg/kg/day).

In an embryo-fetal development study in pregnant rabbits dosed during the period of organogenesis from gestation days 6-18, budesonide produced fetal loss, decreased fetal weight, and skeletal abnormalities at doses 0.5 times the MRHDID (on a mcg/m^2 basis at a maternal subcutaneous dose of 25 mcg/kg/day). In an embryo-fetal development study in pregnant rats dosed during the period of organogenesis from gestation days 6-15, budesonide produced similar adverse fetal effects at doses approximately 5 times the MRHDID (on a mcg/m^2 basis at a maternal subcutaneous dose of 500 mcg/kg/day). In another embryo-fetal development study in pregnant rats, no structural abnormalities or embryocidal effects were seen at doses approximately 2 times the MRHDID (on a mcg/m^2 basis at maternal inhalation doses up to 250 mcg/kg/day).

In a peri-and post-natal development study, rats dosed from gestation day 15 to postpartum day 21, budesonide had no effects on delivery, but did have an effect on growth and development of offspring. Offspring survival was reduced and surviving offspring had decreased mean body weights at birth and during lactation at doses less than 0.2 times the MRHDID and higher (on a mcg/m^2 basis at maternal subcutaneous doses of 20 mcg/kg/day and higher). These findings occurred in the presence of maternal toxicity.

8.2 Lactation

Risk Summary

There are no available data on the effects of PULMICORT RESPULES on the breastfed child or on milk production. Budesonide, like other inhaled corticosteroids, is present in human milk [see Data]. The developmental and health benefits of breastfeeding should be considered along with the mother’s clinical need for PULMICORT RESPULES and any potential adverse effects on the breastfed infant from PULMICORT RESPULES or from the underlying maternal condition.

Data

Human data with budesonide delivered via dry powder inhaler indicates that the total daily oral dose of budesonide available in breast milk to the infant is approximately 0.3% to 1% of the dose inhaled by the mother [see Clinical Pharmacology (12.3)].

8.4 Pediatric Use

Safety and effectiveness in children six months to 12 months of age has been evaluated but not established. Safety and effectiveness in children 12 months to 8 years of age have been established [see Clinical Pharmacology (12.2), Adverse Reactions (6.1)].

A 12-week study in 141 pediatric patients 6 to 12 months of age with mild to moderate asthma or recurrent/persistent wheezing was conducted. All patients were randomized to receive either 0.5 mg or 1 mg of PULMICORT RESPULES or placebo once daily. Adrenal-axis function was assessed with an ACTH stimulation test at the beginning and end of the study, and mean changes from baseline in this variable did not indicate adrenal suppression in patients who received PULMICORT RESPULES versus placebo. However, on an individual basis, 7 patients in this study (6 in the PULMICORT RESPULES treatment arms and 1 in the placebo arm) experienced a shift from having a normal baseline stimulated cortisol level to having a subnormal level at Week 12 [see Clinical Pharmacology (12.2)]. Pneumonia was observed more frequently in patients treated with PULMICORT RESPULES than in patients treated with placebo, (N = 2, 1, and 0) in the PULMICORT RESPULES 0.5 mg, 1 mg, and placebo groups, respectively.

A dose dependent effect on growth was also noted in this 12-week trial. Infants in the placebo arm experienced an average growth of 3.7 cm over 12 weeks compared with 3.5 cm and 3.1 cm in the PULMICORT RESPULES 0.5 mg and 1 mg arms respectively. This corresponds to estimated mean (95% CI) reductions in 12-week growth velocity between placebo and PULMICORT RESPULES 0.5 mg of 0.2 cm (-0.6 to 1.0) and between placebo and PULMICORT RESPULES 1 mg of 0.6 cm (-0.2 to 1.4). These findings support that the use of PULMICORT RESPULES in infants 6 to 12 months of age may result in systemic effects and are consistent with findings of growth suppression in other studies with inhaled corticosteroids.

Controlled clinical studies have shown that inhaled corticosteroids may cause a reduction in growth velocity in pediatric patients. In these studies, the mean reduction in growth velocity was approximately one centimeter per year (range 0.3 to 1.8 cm per year) and appears to be related to dose and duration of exposure. This effect has been observed in the absence of laboratory evidence of hypothalamic-pituitary-adrenal (HPA)-axis suppression, suggesting that growth velocity is a more sensitive indicator of systemic corticosteroid exposure in pediatric patients than some commonly used tests of HPA-axis function. The long-term effects of this reduction in growth velocity associated with orally inhaled corticosteroids, including the impact on final adult height, are unknown. The potential for “catch up” growth following discontinuation of treatment with orally inhaled corticosteroids has not been adequately studied.

In a study of asthmatic children 5-12 years of age, those treated with budesonide administered via a dry powder inhaler 200 mcg twice daily (n=311) had a 1.1-centimeter reduction in growth compared with those receiving placebo (n=418) at the end of one year; the difference between these two treatment groups did not increase further over three years of additional treatment. By the end of four years, children treated with the budesonide dry powder inhaler and children treated with placebo had similar growth velocities. Conclusions drawn from this study may be confounded by the unequal use of corticosteroids in the treatment groups and inclusion of data from patients attaining puberty during the course of the study. The growth of pediatric patients receiving inhaled corticosteroids, including PULMICORT RESPULES, should be monitored routinely (e.g., via stadiometry). The potential growth effects of prolonged treatment should be weighed against clinical benefits obtained and the risks and benefits associated with alternative therapies. To minimize the systemic effects of inhaled corticosteroids, including PULMICORT RESPULES, each patient should be titrated to his/her lowest effective dose [see Dosage and Administration (2), Warnings and Precautions (5.8)].

8.5 Geriatric Use

Of the 215 patients in 3 clinical trials of PULMICORT RESPULES in adult patients, 65 (30%) were 65 years of age or older, while 22 (10%) were 75 years of age or older. No overall differences in safety were observed between these patients and younger patients, and other reported clinical or medical surveillance experience has not identified differences in responses between the elderly and younger patients.

8.6 Hepatic Impairment

Formal pharmacokinetic studies using PULMICORT RESPULES have not been conducted in patients with hepatic impairment. However, since budesonide is predominantly cleared by hepatic metabolism, impairment of liver function may lead to accumulation of budesonide in plasma. Therefore, patients with hepatic disease should be closely monitored.

10 OVERDOSAGE

The potential for acute toxic effects following overdose of PULMICORT RESPULES is low. If inhaled corticosteroids are used at excessive doses for prolonged periods, systemic corticosteroid effects such as hypercorticism or growth suppression may occur [see Warnings and Precautions (5.6)].

11 DESCRIPTION

Budesonide, the active component of PULMICORT RESPULES®, is a corticosteroid designated chemically as (RS)-11β, 16α, 17, 21-tetrahydroxypregna-1, 4-diene-3, 20-dione cyclic 16, 17-acetal with butyraldehyde. Budesonide is provided as a mixture of two epimers (22R and 22S). The empirical formula of budesonide is C25H34O6 and its molecular weight is 430.5. Its structural formula is:

Budesonide is a white to off-white, tasteless, odorless powder that is practically insoluble in water and in heptane, sparingly soluble in ethanol, and freely soluble in chloroform. Its partition coefficient between octanol and water at pH 7.4 is 1.6 x 10^3.

PULMICORT RESPULES is a sterile suspension for inhalation via jet nebulizer and contains the active ingredient budesonide (micronized), and the inactive ingredients disodium edetate, sodium chloride, sodium citrate, citric acid, polysorbate 80, and Water for Injection. Three dose strengths are available in single-dose ampules (Respules™ ampules): 0.25 mg, 0.5 mg, and 1 mg per 2 mL RESPULES ampule. For PULMICORT RESPULES, like all other nebulized treatments, the amount delivered to the lungs will depend on patient factors, the jet nebulizer utilized, and compressor performance. Using the Pari-LC-Jet Plus Nebulizer/Pari Master compressor system, under in vitro conditions, the mean delivered dose at the mouthpiece (% nominal dose) was approximately 17% at a mean flow rate of 5.5 L/min. The mean nebulization time was 5 minutes or less. PULMICORT RESPULES should be administered from jet nebulizers at adequate flow rates, via face masks or mouthpieces [see Dosage and Administration (2)].

12 CLINICAL PHARMACOLOGY

12.1 Mechanism of Action

Budesonide is an anti-inflammatory corticosteroid that exhibits potent glucocorticoid activity and weak mineralocorticoid activity. In standard in vitro and animal models, budesonide has approximately a 200-fold higher affinity for the glucocorticoid receptor and a 1000-fold higher topical anti-inflammatory potency than cortisol (rat croton oil ear edema assay). As a measure of systemic activity, budesonide is 40 times more potent than cortisol when administered subcutaneously and 25 times more potent when administered orally in the rat thymus involution assay. The clinical significance of these findings is unknown.

The activity of PULMICORT RESPULES is due to the parent drug, budesonide. In glucocorticoid receptor affinity studies, the 22R form was two times as active as the 22S epimer. In vitro studies indicated that the two forms of budesonide do not interconvert.

The precise mechanism of corticosteroid actions on inflammation in asthma is not well known. Inflammation is an important component in the pathogenesis of asthma. Corticosteroids have been shown to have a wide range of inhibitory activities against multiple cell types (e.g., mast cells, eosinophils, neutrophils, macrophages, and lymphocytes) and mediators (e.g., histamine, eicosanoids, leukotrienes, and cytokines) involved in allergic- and non-allergic-mediated inflammation. The anti-inflammatory actions of corticosteroids may contribute to their efficacy in asthma.

Studies in asthmatic patients have shown a favorable ratio between topical anti-inflammatory activities and systemic corticosteroid effects over a wide dose range of inhaled budesonide in a variety of formulations and delivery systems including an inhalation-driven, multi-dose dry powder inhaler and the inhalation suspension for nebulization. This is explained by a combination of a relatively high local anti-inflammatory effect, extensive first pass hepatic degradation of orally absorbed drug (85-95%) and the low potency of metabolites (see below).

12.2 Pharmacodynamics

The therapeutic effects of conventional doses of orally inhaled budesonide are largely explained by its direct local action on the respiratory tract. To confirm that systemic absorption is not a significant factor in the clinical efficacy of inhaled budesonide, a clinical study in adult patients with asthma was performed comparing 400 mcg budesonide administered via a pressurized metered dose inhaler with a tube spacer to 1400 mcg of oral budesonide and placebo. The study demonstrated the efficacy of inhaled budesonide but not orally administered budesonide, even though systemic budesonide exposure was comparable for both treatments, indicating that the inhaled treatment is working locally in the lung. Thus, the therapeutic effect of conventional doses of orally inhaled budesonide are largely explained by its direct action on the respiratory tract.

Improvement in the control of asthma symptoms following inhalation of PULMICORT RESPULES can occur within 2-8 days of beginning treatment, although maximum benefit may not be achieved for 4-6 weeks.

Budesonide administered via a dry powder inhaler has been shown in various challenge models (including histamine, methacholine, sodium metabisulfite, and adenosine monophosphate) to decrease bronchial hyperresponsiveness in asthmatic patients. The clinical relevance of these models is not certain.

Pre-treatment with budesonide administered as 1600 mcg daily (800 mcg twice daily) via a dry powder inhaler for 2 weeks reduced the acute (early-phase reaction) and delayed (late-phase reaction) decrease in FEV1 following inhaled allergen challenge.

HPA Axis Effects

The effects of PULMICORT RESPULES on the hypothalamic-pituitary-adrenal (HPA) axis were studied in three, 12-week, double-blind, placebo-controlled studies in 293 pediatric patients, 6 months to 8 years of age, with persistent asthma. For most patients, the ability to increase cortisol production in response to stress, as assessed by the short cosyntropin (ACTH) stimulation test, remained intact with PULMICORT RESPULES treatment at recommended doses. In the subgroup of children age 6 months to 2 years (n=21) receiving a total daily dose of PULMICORT RESPULES equivalent to 0.25 mg (n=5), 0.5 mg (n=5), 1 mg (n=8), or placebo (n=3), the mean change from baseline in ACTH-stimulated cortisol levels showed a decline in peak stimulated cortisol at 12 weeks compared to an increase in the placebo group. These mean differences were not statistically significant compared to placebo. Another 12-week study in 141 pediatric patients 6 to 12 months of age with mild to moderate asthma or recurrent/persistent wheezing was conducted. All patients were randomized to receive either 0.5 mg or 1 mg of PULMICORT RESPULES or placebo once daily. A total of 28, 17, and 31 patients in the PULMICORT RESPULES 0.5 mg, 1 mg, and placebo arms respectively, had an evaluation of serum cortisol levels post-ACTH stimulation both at baseline and at the end of the study. The mean change from baseline to Week 12 ACTH-stimulated minus basal plasma cortisol levels did not indicate adrenal suppression in patients treated with PULMICORT RESPULES versus placebo. However, 7 patients in this study (4 of whom received PULMICORT RESPULES 0.5 mg, 2 of whom received PULMICORT RESPULES 1 mg and 1 of whom received placebo) showed a shift from normal baseline stimulated cortisol level (≥500 nmol/L) to a subnormal level (<500 nmol/L) at Week 12. In 4 of these patients receiving PULMICORT RESPULES, the cortisol values were near the cutoff value of 500 nmol/L.

The effects of PULMICORT RESPULES at doses of 0.5 mg twice daily, and 1 mg and 2 mg twice daily (2 times and 4 times the highest recommended total daily dose, respectively) on 24-hour urinary cortisol excretion were studied in 18 patients between 6 to 15 years of age with persistent asthma in a cross-over study design (4 weeks of treatment per dose level). There was a dose-related decrease in urinary cortisol excretion at 2 and 4 times the recommended daily dose. The two higher doses of PULMICORT RESPULES (1 and 2 mg twice daily) showed statistically significantly reduced (43-52%) urinary cortisol excretion compared to the run-in period. The highest recommended dose of PULMICORT RESPULES, 1 mg total daily dose, did not show statistically significantly reduced urinary cortisol excretion compared to the run-in period.

PULMICORT RESPULES, like other inhaled corticosteroid products, may impact the HPA axis, especially in susceptible individuals, in younger children, and in patients given high doses for prolonged periods [see Warnings and Precautions (5.5)].

12.3 Pharmacokinetics

Absorption:

In asthmatic children 4-6 years of age, the total absolute bioavailability (i.e., lung + oral) following administration of PULMICORT RESPULES via jet nebulizer was approximately 6% of the labeled dose.

In children, a peak plasma concentration of 2.6 nmol/L was obtained approximately 20 minutes after nebulization of a 1 mg dose. Systemic exposure, as measured by AUC and Cmax, is similar for young children and adults after inhalation of the same dose of PULMICORT RESPULES.

Distribution:

In asthmatic children 4-6 years of age, the volume of distribution at steady-state of budesonide was 3 L/kg, approximately the same as in healthy adults. Budesonide is 85-90% bound to plasma proteins, the degree of binding being constant over the concentration range (1-100 nmol/L) achieved with, and exceeding, recommended doses. Budesonide showed little or no binding to corticosteroid-binding globulin. Budesonide rapidly equilibrated with red blood cells in a concentration independent manner with a blood/plasma ratio of about 0.8.

Metabolism:

In vitro studies with human liver homogenates have shown that budesonide is rapidly and extensively metabolized. Two major metabolites formed via cytochrome P450 (CYP) isoenzyme 3A4 (CYP3A4) catalyzed biotransformation have been isolated and identified as 16α-hydroxyprednisolone and 6β-hydroxybudesonide. The corticosteroid activity of each of these two metabolites is less than 1% of that of the parent compound. No qualitative difference between the in vitro and in vivo metabolic patterns has been detected. Negligible metabolic inactivation was observed in human lung and serum preparations.

Excretion/Elimination:

Budesonide is primarily cleared by the liver. Budesonide is excreted in urine and feces in the form of metabolites. In adults, approximately 60% of an intravenous radiolabeled dose was recovered in the urine. No unchanged budesonide was detected in the urine.

In asthmatic children 4-6 years of age, the terminal half-life of budesonide after nebulization is 2.3 hours, and the systemic clearance is 0.5 L/min, which is approximately 50% greater than in healthy adults after adjustment for differences in weight.

Special Populations: No differences in pharmacokinetics due to race, gender, or age have been identified.

Hepatic Insufficiency:

Reduced liver function may affect the elimination of corticosteroids. The pharmacokinetics of budesonide were affected by compromised liver function as evidenced by a doubled systemic availability after oral ingestion. The intravenous pharmacokinetics of budesonide were, however, similar in cirrhotic patients and in healthy adults.

Nursing Mothers:

The disposition of budesonide when delivered by inhalation from a dry powder inhaler at doses of 200 or 400 mcg twice daily for at least 3 months was studied in eight lactating women with asthma from 1 to 6 months postpartum. Systemic exposure to budesonide in these women appears to be comparable to that in non-lactating women with asthma from other studies. Breast milk obtained over eight hours post-dose revealed that the maximum concentration of budesonide for the 400 and 800 mcg doses was 0.39 and 0.78 nmol/L, respectively, and occurred within 45 minutes after dosing. The estimated oral daily dose of budesonide from breast milk to the infant is approximately 0.007 and 0.014 mcg/kg/day for the two dose regimens used in this study, which represents approximately 0.3% to 1% of the dose inhaled by the mother. Budesonide levels in plasma samples obtained from five infants at about 90 minutes after breast-feeding (and about 140 minutes after drug administration to the mother) were below quantifiable levels (<0.02 nmol/L in four infants and <0.04 nmol/L in one infant) [see Use in Specific Populations (8.2)].

Drug-Drug Interactions

Inhibitors of cytochrome P450 enzymes

Ketoconazole: Ketoconazole, a strong inhibitor of cytochrome P450 (CYP) isoenzyme 3A4 (CYP3A4), the main metabolic enzyme for corticosteroids, increased plasma levels of orally ingested budesonide [see Warnings and Precautions (5.12), Drug Interactions (7.1)].

Cimetidine: At recommended doses, cimetidine, a non-specific inhibitor of CYP enzymes, had a slight but clinically insignificant effect on the pharmacokinetics of oral budesonide.

13 NONCLINICAL TOXICOLOGY

13.1 Carcinogenesis, Mutagenesis, Impairment of Fertility

In a two-year study in Sprague-Dawley rats, budesonide caused a statistically significant increase in the incidence of gliomas in male rats at an oral dose of 50 mcg/kg (approximately 0.5 and 0.1 times, respectively, the MRHDID in adults and children 12 months to 8 years of age on a mcg/m^2 basis). No tumorigenicity was seen in male rats at oral doses up to 25 mcg/kg (approximately 0.2 and 0.04 times, respectively, the MRHDID in adults and children 12 months to 8 years of age on a mcg/m^2 basis) and in female rats at oral doses up to 50 mcg/kg (approximately 0.5 and 0.1 times, respectively, MRHDID in adults and children 12 months to 8 years of age on a mcg/m^2 basis). In two additional two-year studies in male Fischer and Sprague-Dawley rats, budesonide caused no gliomas at an oral dose of 50 mcg/kg (approximately 0.5 and 0.1 times, respectively, the MRHDID in adults and children 12 months to 8 years of age on a mcg/m^2 basis). However, in the male Sprague- Dawley rats, budesonide caused a statistically significant increase in the incidence of hepatocellular tumors at an oral dose of 50 mcg/kg (approximately 0.5 and 0.1 times, respectively, the MRHDID in adults and children 12 months to 8 years of age on a mcg/m^2 basis). The concurrent reference corticosteroids (prednisolone and triamcinolone acetonide) in these two studies showed similar findings.

In a 91-week study in mice, budesonide caused no treatment-related carcinogenicity at oral doses up to 200 mcg/kg (approximately equivalent to and 0.1 times, respectively, the MRHDID in adults and children 12 months to 8 years of age on a mcg/m^2 basis).

Budesonide was not mutagenic or clastogenic in six different test systems: Ames Salmonella/microsome plate test, mouse micronucleus test, mouse lymphoma test, chromosome aberration test in human lymphocytes, sex-linked recessive lethal test in Drosophila melanogaster, and DNA repair analysis in rat hepatocyte culture.

Fertility and reproductive performance were unaffected in rats at subcutaneous doses up to 80 mcg/kg approximately equivalent to the MRHDID in adults on a mcg/m2 basis. However, it caused a decrease in prenatal viability and viability in the pups at birth and during lactation, along with a decrease in maternal body-weight gain, at subcutaneous doses of 20 mcg/kg and above approximately 0.2 times than the MRHDID in adults on a mcg/m2 basis. No such effects were noted at 5 mcg/kg (approximately 0.05 times the MRHDID in adults on a mcg/m2 basis).

14 CLINICAL STUDIES

Three double-blind, placebo-controlled, parallel group, randomized U.S. clinical trials of 12-weeks duration each were conducted in 1018 pediatric patients, 6 months to 8 years of age, 657 males and 361 females (798 Caucasians, 140 Blacks, 56 Hispanics, 3 Asians, 21 Others) with persistent asthma of varying disease duration (2 to 107 months) and severity. Doses of 0.25 mg, 0.5 mg, and 1 mg administered either once or twice daily were compared to placebo to provide information about appropriate dosing to cover a range of asthma severity. A Pari-LC-Jet Plus Nebulizer (with a face mask or mouthpiece) connected to a Pari Master compressor was used to deliver PULMICORT RESPULES to patients in the 3 U.S. controlled clinical trials. The co-primary endpoints were nighttime and daytime asthma symptom scores (0-3 scale). Improvements were addressed in terms of the primary efficacy variables of changes from baseline to the double-blind treatment period in nighttime and daytime asthma symptom scores (scale 0-3) as recorded in the patient diaries. Baseline was defined as the mean of the last seven days prior to randomization). The double-blind treatment period was defined as the mean over 12 week treatment period. Each of the five doses discussed below were studied in one or two, but not all three of the U.S. studies.

Results of the 3 controlled clinical trials for recommended dosages of budesonide inhalation suspension (0.25 mg to 0.5 mg once or twice daily, or 1 mg once daily, up to a total daily dose of 1 mg) in 946 patients, 12 months to 8 years of age, are presented below. Statistically significant decreases in nighttime and daytime symptom scores of asthma were observed at PULMICORT RESPULES doses of 0.25 mg once daily (one study), 0.25 mg twice daily, and 0.5 mg twice daily compared to placebo. Use of PULMICORT RESPULES resulted in statistically significant decreases in either nighttime or daytime symptom scores, but not both, at doses of 1 mg once daily, and 0.5 mg once daily (one study). Symptom reduction in response to PULMICORT RESPULES occurred across gender and age. Statistically significant reductions in the need for bronchodilator therapy were also observed at all the doses of PULMICORT RESPULES studied.

Improvements in lung function were associated with PULMICORT RESPULES in the subgroup of patients capable of performing lung function testing. Statistically significant increases were seen in FEV1 [PULMICORT RESPULES 0.5 mg once daily and 1 mg once daily (one study); 0.5 mg twice daily] and morning PEF [PULMICORT RESPULES 1 mg once daily (one study); 0.25 mg twice daily; 0.5 mg twice daily] compared to placebo.

A numerical reduction in nighttime and daytime symptom scores (0-3 scale) of asthma was observed within 2-8 days, although maximum benefit was not achieved for 4-6 weeks after starting treatment. The reduction in nighttime and daytime asthma symptom scores was maintained throughout the 12 weeks of the double-blind trials.

Patients Not Receiving Inhaled Corticosteroid Therapy

The efficacy of PULMICORT RESPULES at doses of 0.25 mg, 0.5 mg, and 1 mg once daily was evaluated in 344 pediatric patients, 12 months to 8 years of age, with mild to moderate persistent asthma (mean baseline nighttime asthma symptom scores of the treatment groups ranged from 1.07 to 1.34) who were not well controlled by bronchodilators alone. The changes from baseline to Weeks 0-12 in nighttime asthma symptom scores are shown in Figure 1. Nighttime asthma symptom scores showed statistically significant decreases in the patients treated with PULMICORT RESPULES compared to placebo. Similar decreases were also observed for daytime asthma symptom scores.

Changes from baseline to the double-blind phase for the budesonide treatment groups compared to placebo were made using analysis of variance techniques. The model included terms for the respective changes from baseline as the dependent variable and terms for treatment, center and treatment by center interaction as exploratory variables (see Figures 1-3).

Figure 1: A 12-Week Trial in Pediatric Patients Not on Inhaled Corticosteroid Therapy Prior to Study Entry. Nighttime Asthma Change from Baseline

p-value – 0.25 mg: 0.001, 0.5 mg: 0.010, 1.0 mg: 0.009

Patients Previously Maintained on Inhaled Corticosteroids

The efficacy of PULMICORT RESPULES at doses of 0.25 mg and 0.5 mg twice daily was evaluated in 133 pediatric asthma patients, 4 to 8 years of age, previously maintained on inhaled corticosteroids (mean FEV1 79.5% predicted; mean baseline nighttime asthma symptom scores of the treatment groups ranged from 1.04 to 1.18; mean baseline dose of beclomethasone dipropionate of 265 mcg/day, ranging between 42 to 1008 mcg/day; mean baseline dose of triamcinolone acetonide of 572 mcg/day, ranging between 200 to 1200 mcg/day). The changes from baseline to Weeks 0-12 in nighttime asthma symptom scores are shown in Figure 2. Nighttime asthma symptom scores showed statistically significant decrease in patients treated with PULMICORT RESPULES compared to placebo. Similar decreases were also observed for daytime asthma symptom scores.

Statistically significant increases in FEV1 compared to placebo were observed with PULMICORT RESPULES at a dose of 0.5 mg twice daily and in morning PEF for both doses (0.25 mg and 0.5 mg twice daily).

Figure 2: A 12-Week Trial in Pediatric Patients Previously Maintained on Inhaled Corticosteroid Therapy Prior to Study Entry. Nighttime Asthma Change from Baseline

p-values: 0.25 mg: 0.022, 0.5 mg: 0.021

Patients Receiving Once-Daily or Twice-Daily Dosing

The efficacy of PULMICORT RESPULES at doses of 0.25 mg once daily, 0.25 mg twice daily, 0.5 mg twice daily, and 1 mg once daily, was evaluated in 469 pediatric patients 12 months to 8 years of age (mean baseline nighttime asthma symptom scores of the treatment groups ranged from 1.13 to 1.31). Approximately 70% were not previously receiving inhaled corticosteroids. The changes from baseline to Weeks 0-12 in nighttime asthma symptom scores are shown in Figure 3. PULMICORT RESPULES at doses of 0.25 mg and 0.5 mg twice daily, and 1 mg once daily, demonstrated statistically significant decreases in nighttime asthma symptom scores compared to placebo. Similar decreases were also observed for daytime asthma symptom scores.

PULMICORT RESPULES at a dose of 0.5 mg twice daily resulted in statistically significant increases compared to placebo in FEV1, and at doses of 0.25 mg and 0.5 mg twice daily and 1 mg once daily statistically significant increases in morning PEF.

The evidence supports the efficacy of the same nominal dose of PULMICORT RESPULES administered on either a once-daily or twice-daily schedule. However, when all measures are considered together, the evidence is stronger for twice-daily dosing [see Dosage and Administration (2)].

Figure 3: A 12-Week Trial in Pediatric Patients Either Maintained on Bronchodilators Alone or Inhaled Corticosteroid Therapy Prior to Study Entry. Nighttime Asthma Change from Baseline

p-values: 0.25 mg qd: 0.121, 0.25 mg bid: <0.001, 0.5 mg bid: 0.003, 1.0 mg qd: 0.005

16 HOW SUPPLIED/STORAGE AND HANDLING

PULMICORT RESPULES is supplied in sealed aluminum foil envelopes containing one plastic strip of five single-dose RESPULES ampules together with patient instructions for use. There are 30 RESPULES ampules in a carton. Each single-dose RESPULES ampule contains 2 mL of sterile liquid suspension.

PULMICORT RESPULES is available in three strengths, each containing 2 mL:

NDC 0186–1988–04 | 0.25 mg/2 mL
NDC 0186–1989–04 | 0.5 mg/2 mL
NDC 0186–1990–04 | 1 mg/2 mL

PULMICORT RESPULES should be stored upright at controlled room temperature 20-25°C (68-77°F) [see USP], and protected from light. When an envelope has been opened, the shelf life of the unused RESPULES ampules is 2 weeks when protected. After opening the aluminum foil envelope, the unused RESPULES ampules should be returned to the aluminum foil envelope to protect them from light. Any opened RESPULES ampule must be used promptly. Gently shake the RESPULES ampule using a circular motion before use. Keep out of reach of children. Do not freeze.

17 PATIENT COUNSELING INFORMATION

17.1 Administration with a Jet Nebulizer

Patients should be advised that PULMICORT RESPULES should be administered with a jet nebulizer connected to a compressor with an adequate air flow, equipped with a mouthpiece or suitable face mask. Ultrasonic nebulizers are not suitable for the adequate administration of PULMICORT RESPULES and, therefore, are not recommended. The effects of mixing PULMICORT RESPULES with other nebulizable medications have not been adequately assessed. PULMICORT RESPULES should be administered separately in the nebulizer [see Dosage and Administration (2)].

17.2 Oral Candidiasis

Patients should be advised that localized infections with Candida albicans occurred in the mouth and pharynx in some patients. If oropharyngeal candidiasis develops, it should be treated with appropriate local or systemic (i.e., oral) antifungal therapy while still continuing therapy with PULMICORT RESPULES, but at times therapy with PULMICORT RESPULES may need to be temporarily interrupted under close medical supervision. Rinsing the mouth after inhalation is advised [see Warnings and Precautions (5.1)].

17.3 Not for Acute Symptoms

PULMICORT RESPULES is not meant to relieve acute asthma symptoms and extra doses should not be used for that purpose. Acute symptoms should be treated with an inhaled, short-acting beta2-agonist such as albuterol. (The healthcare professional should provide that patient with such medication and instruct the patient in how it should be used). Patients should be instructed to notify their healthcare professional immediately if they experience any of the following:

- Decreasing effectiveness of inhaled, short-acting beta2- agonists
- Need for more inhalations than usual of inhaled, short-acting beta2-agonists
- Significant decrease in lung function as outlined by the physician

Patients should not stop therapy with PULMICORT RESPULES without physician/provider guidance since symptoms may recur after discontinuation [see Warnings and Precautions (5.2)].

17.4 Hypersensitivity Including Anaphylaxis

Hypersensitivity reactions including anaphylaxis, rash, contact dermatitis, urticaria, angioedema, and bronchospasm have been reported with use of PULMICORT RESPULES. Discontinue PULMICORT RESPULES if such reactions occur [see Contraindications (4), Warning and Precautions (5.3)].

17.5 Immunosuppression

Patients who are on immunosuppressant doses of corticosteroids should be warned to avoid exposure to chickenpox or measles and, if exposed, to consult their physician without delay. If exposure to such a person occurs, and the child has not had chicken pox or been properly vaccinated, a physician should be consulted without delay. Patients should be informed of potential worsening of existing tuberculosis, fungal, bacterial, viral, or parasitic infections, or ocular herpes simplex [see Warnings and Precautions (5.4)].

17.6 Hypercorticism and Adrenal Suppression

Patients should be advised that PULMICORT RESPULES may cause systemic corticosteroid effects of hypercorticism and adrenal suppression. Additionally, patients should be instructed that deaths due to adrenal insufficiency have occurred during and after transfer from systemic corticosteroids. Patients should taper slowly from systemic corticosteroids if transferring to PULMICORT RESPULES [see Warnings and Precautions (5.6)].

17.7 Reduction in Bone Mineral Density

Patients who are at an increased risk for decreased BMD should be advised that the use of corticosteroids may pose an additional risk [see Warnings and Precautions (5.7)].

17.8 Reduced Growth Velocity

Patients should be informed that orally inhaled corticosteroids, including PULMICORT RESPULES, may cause a reduction in growth velocity when administered to pediatric patients. Healthcare professionals should closely follow the growth of children and adolescents taking corticosteroids by any route [see Warnings and Precautions (5.8)].

17.9 Ocular Effects

Long-term use of inhaled corticosteroids may increase the risk of some eye problems (cataracts or glaucoma); regular eye examinations should be considered [see Warnings and Precautions (5.9)].

17.10 Use Daily

Patients should be advised to use PULMICORT RESPULES at regular intervals once or twice a day, since its effectiveness depends on regular use. Maximum benefit may not be achieved for 4 to 6 weeks or longer after starting treatment. If symptoms do not improve in that time frame or if the condition worsens, patients should be instructed to contact their healthcare professional.

See accompanying Patient Information and Instructions for Use.

Patient Information and Instructions for Use

PULMICORT RESPULES (bew DEH so nide)

(budesonide) inhalation suspension

2 mL ampules containing 0.25 mg, 0.5 mg, or 1 mg

For inhalation only.

Do not swallow.

Only use PULMICORT RESPULES with a jet nebulizer machine that is connected to an air compressor. Do not use with an ultrasonic nebulizer.

Read the Patient Information that comes with PULMICORT RESPULES before your child starts using it and each time you get a refill. There may be new information. This information does not take the place of talking with your healthcare provider about your child’s medical condition or treatment. If you have any questions about PULMICORT RESPULES, ask your healthcare provider or pharmacist.

What is PULMICORT RESPULES?

PULMICORT RESPULES is an inhaled corticosteroid medicine. PULMICORT RESPULES is a long-term maintenance medicine used to control and prevent asthma symptoms in children ages 12 months to 8 years.

Inhaled corticosteroids help to decrease inflammation in the lungs. Inflammation in the lungs can lead to asthma symptoms. PULMICORT RESPULES helps reduce swelling and inflammation in the lungs, and helps keep the airways open to reduce asthma symptoms.

PULMICORT RESPULES does not treat the sudden symptoms (wheezing, cough, shortness of breath, and chest pain or tightness) of an asthma attack. Always have a short-acting beta2-agonist medicine (rescue inhaler) with you to treat sudden symptoms. If your child does not have an inhaled, short-acting bronchodilator, ask your healthcare provider to have one prescribed for your child.

It is not known if PULMICORT RESPULES is safe or effective in children younger than 12 months or older than 8 years.

Who should not use PULMICORT RESPULES?

Do not use PULMICORT RESPULES:

- to treat sudden symptoms of asthma
- if your child is allergic to budesonide or any of the ingredients in PULMICORT RESPULES. See the end of this leaflet for a complete list of ingredients in PULMICORT RESPULES.

What should I tell my healthcare provider before using PULMICORT RESPULES?

Before your child uses PULMICORT RESPULES, tell your healthcare provider if your child:

- has an allergy. See the section “Who should not use PULMICORT RESPULES?” There is a complete list of ingredients in PULMICORT RESPULES at the end of this leaflet.
- has or recently had chicken pox or measles, or has recently been near anyone with chicken pox or measles.
- has or had tuberculosis of the respiratory tract.
- has certain kinds of infections that have not been treated, including:
  - fungal infections
  - bacterial infections
  - viral infections
  - parasitic infections
  - herpes simplex infection of the eye (ocular herpes simplex)

PULMICORT RESPULES may not be right for children who have had any of these types of infections.

- has decreased bone mineral density (bone strength). Your child is at risk for decreased bone mineral density if he or she:
  - is inactive for a long period of time
  - has a family history of osteoporosis
  - does not eat well (poor nutrition)
  - takes bone thinning medicines (such as anticonvulsant medicines or corticosteroids) for a long time.
- has an eye problem such as increased pressure in the eye, glaucoma or cataracts.
- has liver problems.
- is planning to have surgery.
- has any other medical conditions.
- is pregnant or plans to become pregnant. It is not known if PULMICORT RESPULES will harm your unborn baby.
- is breast-feeding or plans to breast-feed. PULMICORT RESPULES can pass into breast milk. You and your healthcare provider should decide if you will use PULMICORT RESPULES or breast-feed.

Tell your healthcare provider about all the medicine your child takes, including prescription and non-prescription medicines, vitamins, and herbal supplements.

Using PULMICORT RESPULES with certain other medicines may affect each other causing side effects. Especially tell your healthcare provider if your child takes:

- corticosteroids
- anti-seizure medicine (anticonvulsants)
- medicines that suppress the immune system (immunosuppressant)
- ketoconazole (Nizoral)
- certain medicines that can affect how your liver breaks down medicine

Ask your healthcare provider or pharmacist for a list of these medicines, if you are not sure.

Know the medicines your child takes. Keep a list of them and show it to your healthcare provider and pharmacist when your child gets a new medicine.

How should I use PULMICORT RESPULES?

- Use PULMICORT RESPULES exactly as prescribed by your healthcare provider. Your child must use PULMICORT RESPULES regularly for it to work.
- PULMICORT RESPULES comes in three strengths. Your healthcare provider has prescribed the strength that is best for your child.
- Do not stop using PULMICORT RESPULES, and do not change your child’s dose of PULMICORT RESPULES without talking to your healthcare provider.
- PULMICORT RESPULES is for inhaled use only. Use PULMICORT RESPULES with a jet nebulizer connected to an air compressor set up with a mouthpiece or face mask. Do not use an ultrasonic nebulizer to give PULMICORT RESPULES.
- Do not mix PULMICORT RESPULES with other nebulizer medicines. If your child uses another medicine by inhalation to treat asthma, talk with your healthcare provider for instructions on when to use the other medicine.
- If your child misses a dose, just give the next regularly scheduled dose when it is due. Do not use PULMICORT RESPULES more often than has been prescribed.
- Improvement in the control of asthma symptoms with PULMICORT RESPULES can occur within 2-8 days. It may take up to 4-6 weeks before maximum improvement is seen.
- Make sure your child always has a short-acting beta2-agonist medicine with him or her. Your child should use the short-acting beta2-agonist medicine for breathing problems between doses of PULMICORT RESPULES or if a sudden asthma attack happens. Call your healthcare provider right away if:
  - the short-acting rescue medicine does not work as well for relieving asthma symptoms.
  - your child needs to use the short-acting rescue medicines more often than usual.
  - your child’s breathing problems worsen with PULMICORT RESPULES
- Rinse your child’s mouth with water and have him or her spit the water out after each PULMICORT RESPULES treatment. Do not swallow the water. This will lessen the chance of getting a fungal infection (thrush) in the mouth.
- If your child has used long-term corticosteroids and the dose is now being lowered or stopped, a warning card should be carried stating that your child may need corticosteroids during times of stress or during an asthma attack that does not get better with bronchodilator medicines.
- Your healthcare provider may check your child’s blood, breathing and do eye exams while using PULMICORT RESPULES.
- Read the Patient Information and Instructions for Use at the end of this leaflet for detailed instructions about how to use PULMICORT RESPULES.

What are the possible side effects of PULMICORT RESPULES?

PULMICORT RESPULES may cause serious side effects including:

- Thrush (candida), a fungal infection in your mouth and throat. Tell your healthcare provider if your child has any redness or white colored patches in the mouth or throat.
- Worsening of asthma or sudden asthma attacks.
- Allergic reactions. Tell your healthcare provider or get medical help right away if your child has:
  - skin rash, redness or swelling
  - severe itching
  - swelling of the face, mouth and tongue
  - trouble breathing or swallowing
  - chest pain
  - anxiety (feeling of doom)
- Immune system effects and a higher chance of infections. Your child is more likely to get infections when taking medicines that weaken the immune system. Symptoms of infection may include: fever, pain, aches, chills, feeling tired, nausea and vomiting. Tell your healthcare provider about any signs of infection while your child uses PULMICORT RESPULES.
- Adrenal insufficiency. Adrenal insufficiency is a condition in which the adrenal glands do not make enough steroid hormones. Symptoms of adrenal insufficiency include tiredness, weakness, nausea and vomiting, and low blood pressure.
- Decrease in bone mineral density (bone strength). Your healthcare provider may want to check your child for this during treatment with PULMICORT RESPULES.
- Slowed or delayed growth problems. Your child’s healthcare provider may want to monitor your child’s growth while using PULMICORT RESPULES.
- Eye problems, including glaucoma and cataracts. Your child’s healthcare provider may suggest eye exams while using PULMICORT RESPULES.
- Increased wheezing right after taking PULMICORT RESPULES. Always have a fast-acting inhaled bronchodilator medicine with you to treat sudden wheezing.

Call your healthcare provider or get medical help right away if your child has any of the serious side effects listed above.

The most common side effects of PULMICORT RESPULES include:

- respiratory infections. Symptoms may include stuffy nose, sore nose and throat.
- runny nose
- cough
- viral infections
- viral irritation and inflammation of the stomach and intestine (gastroenteritis). Gastroenteritis symptoms may include: stomach area pain, diarrhea, nausea and vomiting, and loss of appetite.
- ear infections
- nosebleed
- pink eye (conjunctivitis)
- rash

Tell your healthcare provider if your child has any side effect that bothers him or her or that does not go away. For more information, ask your healthcare provider or pharmacist.

Call your healthcare provider for medical advice about side effects. You may report side effects to AstraZeneca at 1-800-236-9933 or the FDA at 1-800-FDA-1088 or www.fda.gov/medwatch.

How should I store PULMICORT RESPULES?

- Store PULMICORT RESPULES in an upright position between 68°F to 77°F (20°C to 25°C).
- Keep PULMICORT RESPULES in the aluminium foil envelope to protect from light until ready to use.
- After a PULMICORT RESPULES ampule is opened it should be used right away.
- PULMICORT RESPULES ampules can be stored for 2 weeks after opening the protective aluminium foil envelope.
- Throw away PULMICORT RESPULES ampules if not used within 2 weeks of opening the protective aluminium foil envelope.
- Do not refrigerate or freeze.

Keep PULMICORT RESPULES and all medicines out of the reach of children.

General Information about PULMICORT RESPULES

Medicines are sometimes prescribed for conditions other than those listed in a Patient Information leaflet. Do not use PULMICORT RESPULES for a condition for which it was not prescribed. Do not give PULMICORT RESPULES to other people, even if they have the same symptoms that you have. It may harm them.

This Patient Information leaflet summarizes the most important information about PULMICORT RESPULES. If you would like more information, talk with your healthcare provider. You can ask your pharmacist or healthcare provider for information about PULMICORT RESPULES that is written for health professionals.

For more information, go to www.pulmicortrespules.com or call AstraZeneca at 1-800-236-9933.

What are the ingredients in PULMICORT RESPULES?

Active ingredient: budesonide

Inactive ingredients: disodium edetate, sodium chloride, sodium citrate, citric acid, polysorbate 80 and water for injection.

Patient Instructions for Use

Important:

PULMICORT RESPULES is only for use with a jet nebulizer machine. Make sure you know how to use your jet nebulizer machine before your child uses PULMICORT RESPULES.

PULMICORT RESPULES is a liquid that is turned into a mist by a nebulizer and inhaled into the lungs.

The face mask should be properly adjusted to optimize delivery and to avoid exposing the eyes to the nebulized medication. Corticosteroid effects on the skin can be avoided if the face is washed after the use of a face mask.

1. PULMICORT RESPULES come in a sealed protective aluminium foil envelope.
2. Do not open the sealed pouch until you are ready to use a dose of PULMICORT RESPULES.
3. Open the sealed foil envelope along the dotted line and take out 1 single-dose ampule from the strip. See Figure 1.
4. Record the date that you opened the foil on the back of the envelope in the space provided.

Return the unopened PULMICORT RESPULES® ampules on the strip back into the foil envelope before storing.

Figure 1

2. Gently shake the PULMICORT RESPULES ampule using a circular motion as shown in Figure 2.

Figure 2

3. Hold the PULMICORT RESPULES ampule upright without squeezing the ampule and open by twisting off the top as shown in Figure 3.

Figure 3

4. Place the open end of the PULMICORT RESPULES ampule into the nebulizer cup (reservoir) and slowly squeeze all of the medicine from the ampule into the nebulizer medicine cup as shown in Figure 4. Throw away the empty ampule.

Figure 4

5. Use your jet nebulizer as directed.

Revised: 10/16

©AstraZeneca 2007, 2010, 2016, 2019

Manufactured for: AstraZeneca Pharmaceuticals LP, Wilmington, DE 19850

By: AstraZeneca AB, Södertälje, Sweden

Product of Sweden

All trademarks are the property of the AstraZeneca group of companies.

PACKAGE/LABEL PRINCIPAL DISPLAY PANEL – 0.25 mg/2 mL

NDC 0186-1988-04

Pulmicort Respules®

(budesonide inhalation suspension)

FOR INHALATION ONLY.

Rx only

Each single-dose Respules™ ampule delivers 2 mL of a

sterile suspension containing 0.25 mg of micronized

budesonide plus disodium edetate, sodium chloride,

polysorbate 80, citric acid, sodium citrate and Water for

Injection.

Once a RESPULES ampule is opened, use the contents

immediately.

For use only in a jet nebulizer. Do NOT use in an

ultrasonic nebulizer.

PACKAGE/LABEL PRINCIPAL DISPLAY PANEL – 0.5 mg/2 mL

NDC 0186-1989-04

Pulmicort Respules®

(budesonide inhalation suspension)

FOR INHALATION ONLY.

Rx only

Each single-dose Respules™ ampule delivers 2 mL of a

sterile suspension containing 0.5 mg of micronized

budesonide plus disodium edetate, sodium chloride,

polysorbate 80, citric acid, sodium citrate and Water for

Injection.

Once a RESPULES ampule is opened, use the contents

immediately.

For use only in a jet nebulizer. Do NOT use in an

ultrasonic nebulizer.

PACKAGE/LABEL PRINCIPAL DISPLAY PANEL 1 mg/2 mL

NDC 0186-1990-04

Pulmicort Respules®

(budesonide inhalation suspension)

FOR INHALATION ONLY.

Rx only

Each single-dose Respules™ ampule delivers 2 mL of a

sterile suspension containing 1 mg of micronized

budesonide plus disodium edetate, sodium chloride,

polysorbate 80, citric acid, sodium citrate and Water for

Injection.

Once a RESPULES ampule is opened, use the contents

immediately.

For use only in a jet nebulizer. Do NOT use in an

ultrasonic nebulizer.